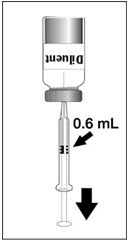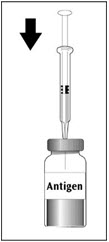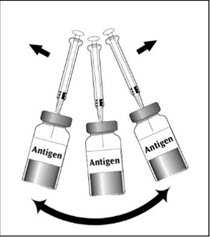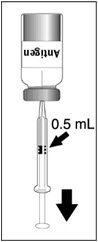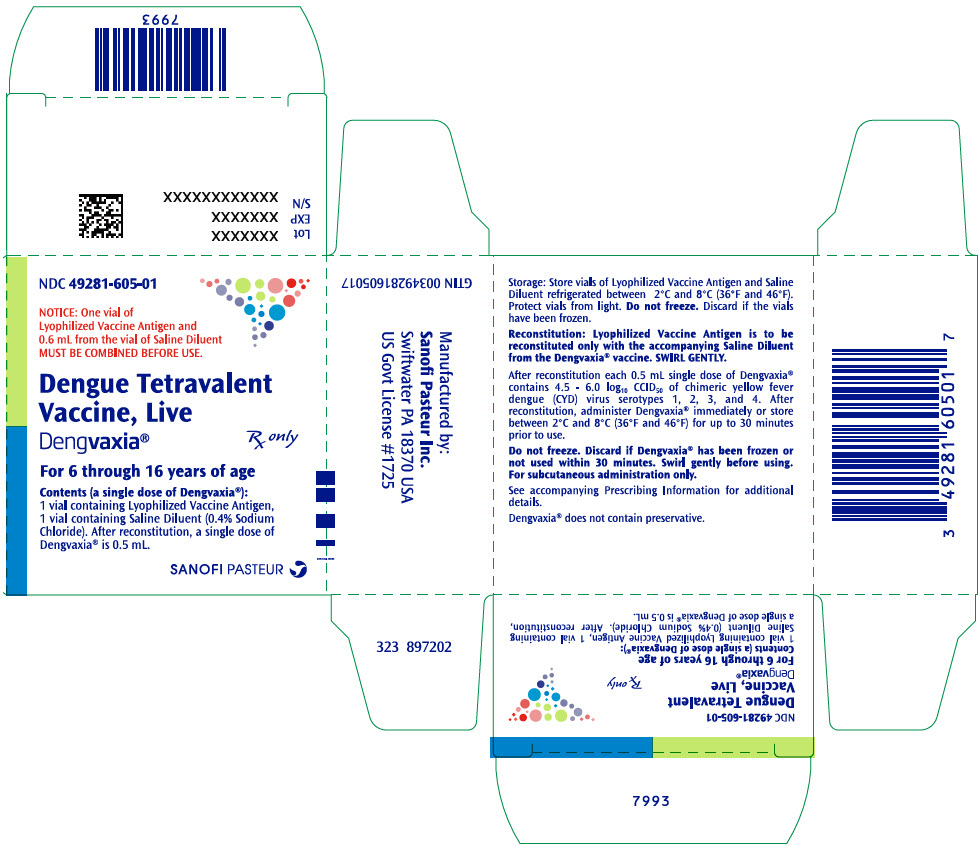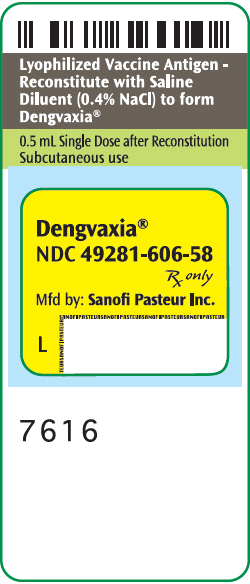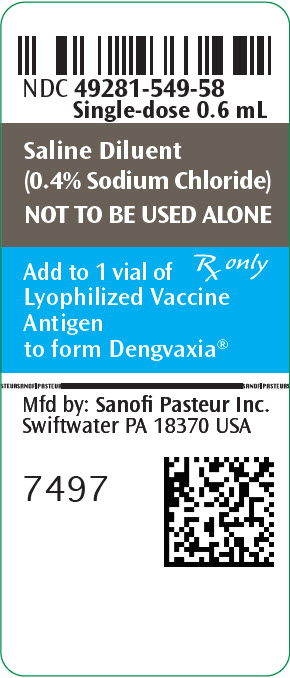 DRUG LABEL: Dengvaxia
NDC: 49281-605 | Form: KIT | Route: SUBCUTANEOUS
Manufacturer: Sanofi Pasteur Inc.
Category: other | Type: VACCINE LABEL
Date: 20250813

ACTIVE INGREDIENTS: DENGUE-YELLOW FEVER CHIMERIC VIRUS SEROTYPE 1 LIVE (ATTENUATED) ANTIGEN 100000 [CCID_50]/0.5 mL; DENGUE-YELLOW FEVER CHIMERIC VIRUS SEROTYPE 2 LIVE (ATTENUATED) ANTIGEN 100000 [CCID_50]/0.5 mL; DENGUE-YELLOW FEVER CHIMERIC VIRUS SEROTYPE 3 LIVE (ATTENUATED) ANTIGEN 100000 [CCID_50]/0.5 mL; DENGUE-YELLOW FEVER CHIMERIC VIRUS SEROTYPE 4 LIVE (ATTENUATED) ANTIGEN 100000 [CCID_50]/0.5 mL
INACTIVE INGREDIENTS: AMINO ACIDS, ESSENTIAL 0.56 mg/0.5 mL; AMINO ACIDS, SOURCE UNSPECIFIED 0.2 mg/0.5 mL; ARGININE HYDROCHLORIDE 2.5 mg/0.5 mL; SUCROSE 18.75 mg/0.5 mL; TREHALOSE DIHYDRATE 13.75 mg/0.5 mL; SORBITOL 9.38 mg/0.5 mL; TROMETHAMINE 0.18 mg/0.5 mL; UREA 0.6 mg/0.5 mL; SODIUM CHLORIDE 2 mg/0.5 mL; SODIUM CHLORIDE

HIGHLIGHTS OF PRESCRIBING INFORMATION

These highlights do not include all the information needed to use DENGVAXIA safely and effectively. See full prescribing information for DENGVAXIA.
DENGVAXIA (Dengue Tetravalent Vaccine, Live)
Suspension for Subcutaneous Injection
Initial U.S. Approval: 2019

RECENT MAJOR CHANGES

Indications and Usage (1) | 07/2023
Warnings and Precautions (5.1) | 07/2023

1 INDICATIONS AND USAGE

DENGVAXIA is a vaccine indicated for the prevention of dengue disease caused by dengue virus serotypes 1, 2, 3 and 4. DENGVAXIA is approved for use in individuals 6 through 16 years of age with laboratory-confirmed previous dengue infection and living in endemic areas.

Limitations of use:

- DENGVAXIA is not approved for use in individuals younger than 6 years of age. These individuals, regardless of previous infection by dengue virus, are at increased risk of severe and hospitalized dengue disease following vaccination with DENGVAXIA and subsequent infection with any dengue virus serotype. (5.1)
- DENGVAXIA is not approved for use in individuals not previously infected by any dengue virus serotype or for whom this information is unknown. Those not previously infected are at increased risk for severe dengue disease when vaccinated and subsequently infected with dengue virus. (5.2) Previous dengue infection can be assessed through a medical record of a previous laboratory-confirmed dengue infection or through serological testing prior to vaccination. (1)
- The safety and effectiveness of DENGVAXIA have not been established in individuals living in dengue nonendemic areas who travel to dengue endemic areas. (1)

2 DOSAGE AND ADMINISTRATION

Three doses (0.5 mL each) 6 months apart (at month 0, 6, and 12). (2.1)

3 DOSAGE FORMS AND STRENGTHS

Suspension for injection (0.5 mL) supplied as a lyophilized powder to be reconstituted with the supplied diluent. (3)

4 CONTRAINDICATIONS

- A history of severe allergic reaction to a previous dose of DENGVAXIA or to any component of DENGVAXIA. (4.1)
- Immunocompromised individuals. (4.2)

5 WARNINGS AND PRECAUTIONS

- In persons younger than 6 years of age, regardless of previous infection by dengue virus, an increased risk of severe and hospitalized dengue disease can occur following vaccination with DENGVAXIA and subsequent infection with any dengue virus serotype. (5.1)
- In persons not previously infected by dengue virus, an increased risk of severe dengue disease can occur following vaccination with DENGVAXIA and subsequent infection with any dengue virus serotype. (5.2)
- There is no FDA-cleared test available to determine a previous dengue infection. (5.2)

6 ADVERSE REACTIONS

The most frequently reported adverse reactions regardless of the dengue serostatus prior to vaccination in ages 9 through 16 years were headache (40%), injection site pain (32%), malaise (25%), asthenia (25%), and myalgia (29%).

The most frequently reported adverse reactions regardless of the dengue serostatus prior to vaccination in ages 6 through 8 years were headache (27%), injection site pain (28%), malaise (19%), asthenia (13%), and myalgia (15%). (6.1)

To report SUSPECTED ADVERSE REACTIONS, contact Pharmacovigilance Department, Sanofi Pasteur Inc., Discovery Drive, Swiftwater, PA 18370 at 1-800-822-2463 (1-800-VACCINE) or VAERS at 1-800-822-7967 or http://vaers.hhs.gov.

7 DRUG INTERACTIONS

False negative tuberculin purified protein derivative (PPD) test results may occur within 1 month following vaccination with DENGVAXIA. (7.2)

FULL PRESCRIBING INFORMATION

1 INDICATIONS AND USAGE

DENGVAXIA® (Dengue Tetravalent Vaccine, Live) is a vaccine indicated for the prevention of dengue disease caused by dengue virus serotypes 1, 2, 3, and 4. DENGVAXIA is approved for use in individuals 6 through 16 years of age with laboratory-confirmed previous dengue infection and living in endemic areas.

Limitations of use

- DENGVAXIA is not approved for use in individuals younger than 6 years of age. These individuals, regardless of previous infection by dengue virus, are at increased risk of severe and hospitalized dengue disease following vaccination with DENGVAXIA and subsequent infection with any dengue virus serotype. [See Warnings and Precautions (5.1).]
- DENGVAXIA is not approved for use in individuals not previously infected by any dengue virus serotype or for whom this information is unknown. Those not previously infected are at increased risk for severe dengue disease when vaccinated and subsequently infected with dengue virus. [See Warnings and Precautions (5.1).] Previous dengue infection can be assessed through a medical record of a previous laboratory-confirmed dengue infection or through serological testing prior to vaccination.
- The safety and effectiveness of DENGVAXIA have not been established in individuals living in dengue nonendemic areas who travel to dengue endemic areas.

2 DOSAGE AND ADMINISTRATION

For subcutaneous use only.

2.1 Dose

Three doses (0.5 mL each) 6 months apart (at month 0, 6, and 12).

2.2 Preparation

The package contains a vial of lyophilized vaccine antigen and a vial of saline diluent (0.4% NaCl).

After removing the "flip-off" caps, cleanse the lyophilized vaccine antigen and diluent vial stoppers with a suitable germicide. Do not remove the vial stoppers or metal seals holding them in place.

To reconstitute DENGVAXIA, use a sterile needle and syringe to withdraw 0.6 mL from the diluent vial and inject it into the vial of the lyophilized vaccine antigen. Swirl the vial gently.

Changing needles between withdrawing the vaccine from the vial and injecting it into a recipient is not necessary unless the needle has been damaged or contaminated.

Figure 1

Figure 2

Figure 3

Figure 4

Insert the syringe needle through the stopper of the vial of diluent and withdraw 0.6 mL liquid content.

Insert the syringe needle through the stopper of the vial of lyophilized vaccine antigen and inject the liquid into the vial.

Swirl vial gently. The syringe needle is not removed while swirling the vial.

After reconstitution, withdraw 0.5 mL.
DENGVAXIA should be used immediately after reconstitution.

After reconstitution, the suspension is colorless and may develop trace amounts of white to translucent endogenous proteinaceous particles. [See Description (11).]

Parenteral drug products should be inspected visually for particulate matter and discoloration prior to administration, whenever solution and container permit. Discard the vial if the solution is cloudy or contains particles other than trace amounts of white to translucent particles.

Discard reconstituted vaccine if not used within 30 minutes. [See How Supplied/Storage and Handling (16.2).]

DENGVAXIA should not be mixed in the same syringe with other parenteral products.

2.3 Administration

After reconstitution, withdraw 0.5 mL of DENGVAXIA and administer subcutaneously immediately or store refrigerated at 2°C to 8°C (36°F to 46°F) and use within 30 minutes. Do not administer DENGVAXIA by intramuscular injection.

3 DOSAGE FORMS AND STRENGTHS

DENGVAXIA is a suspension for injection (supplied as a lyophilized powder to be reconstituted with the supplied diluent, 0.4% NaCl). A single dose, after reconstitution, is 0.5 mL.

4 CONTRAINDICATIONS

4.1 Hypersensitivity

Do not administer DENGVAXIA to individuals with a history of severe allergic reaction to a previous dose of DENGVAXIA or to any component of DENGVAXIA. [See Description (11).]

4.2 Immunocompromised Individuals

Do not administer DENGVAXIA to individuals with severe immunodeficiency or immunosuppression due to disease or therapy.

5 WARNINGS AND PRECAUTIONS

5.1 Increased Risk of Severe Dengue Disease Following DENGVAXIA in Persons Younger than 6 Years of Age Regardless of Previous Infection with Dengue Virus

DENGVAXIA is not approved for use in individuals younger than 6 years of age. In persons younger than 6 years of age regardless of previous infection by dengue virus, an increased risk of severe and hospitalized dengue disease can occur following vaccination with DENGVAXIA and subsequent infection with any dengue virus serotype. [See Use in Specific Populations (8.4)]

5.2 Increased Risk of Severe Dengue Disease Following DENGVAXIA in Persons of Any Age Not Previously Infected with Dengue Virus

In unvaccinated individuals, first dengue infections rarely cause severe dengue, while second dengue infections with a different serotype are associated with an increased risk of severe dengue. DENGVAXIA administration to individuals not previously infected by dengue virus is associated with an increased risk of severe dengue disease when the vaccinated individual is subsequently infected with any dengue virus serotype. Therefore, healthcare professionals must evaluate individuals for prior dengue infection to avoid vaccinating individuals who have not been previously infected by dengue virus.

Previous infection by dengue virus can be evaluated through a medical record of previous laboratory-confirmed dengue infection or through serotesting prior to vaccination.

There is no FDA cleared test available to determine a previous dengue infection. Available non-FDA cleared tests may yield false positive results (e.g., due to cross-reactivity with other flaviviruses).

5.3 Management of Acute Allergic Reactions

DENGVAXIA may cause hypersensitivity reactions, including anaphylaxis. Appropriate medical treatment and supervision must be available following administration of DENGVAXIA.

5.4 Limitations of Vaccine Effectiveness

Vaccination with DENGVAXIA may not protect all individuals. It is recommended to continue personal protection measures against mosquito bites after vaccination.

5.5 Syncope

Syncope (fainting) can occur following, or even before, vaccination with DENGVAXIA as a psychogenic response to injection with a needle. Procedures should be in place to prevent injury from falling and to manage syncopal reactions.

6 ADVERSE REACTIONS

6.1 Clinical Trials Experience

Because clinical trials are conducted under widely varying conditions, adverse reaction rates observed in the clinical trials of a vaccine cannot be directly compared to rates in the clinical trials of another vaccine and may not reflect the rates observed in practice.

The safety of DENGVAXIA in subjects 6 through 16 years of age was evaluated in 12 randomized, placebo-controlled, multicenter clinical trials with at least 28 days of follow-up conducted primarily in dengue endemic regions including Asia-Pacific and Latin American countries. In these studies, a total of 22,924 subjects 6 through 16 years of age received at least one dose of DENGVAXIA and 10,668 received placebo (0.9% sodium chloride). Overall, 51.6% of trial participants who received DENGVAXIA or placebo were female. Racial groups were reported as 27% Asian, 11.9% American Indian or Alaska native, 5.8% Caucasian, 2.3% black, and 53% as other. In the largest study (Study 1, NCT01374516; N = 20,869) conducted in four Latin American countries and Puerto Rico, most subjects (99.9%) reported Hispanic ethnicity. All studies enrolled subjects irrespective of evidence of previous dengue infection.

Solicited Adverse Reactions

In two multi-center, observer-blind, randomized (2:1), placebo-controlled trials conducted in four Latin American countries and Puerto Rico (Study 1, NCT01374516; subjects 9 through 16 years of age) and in five Asia-Pacific countries (Study 2, NCT01373281; subjects 6 through 14 years of age), 2,000 subjects in Study 1 and 1,310 subjects in Study 2 (out of a total of 20,869 subjects and 10,278 subjects respectively) were recruited during the first 2 months of enrollment for inclusion in the reactogenicity subset. Solicited adverse reactions were recorded daily for 14 days following each vaccination.

Table 1 and Table 2 present the frequency and severity of solicited injection site reactions reported within 7 days and systemic adverse reactions reported within 14 days following receipt of DENGVAXIA or placebo.

Table 1: Percentages of Subjects with Solicited Injection Site Reactions within 7 Days and Systemic Adverse Reactions within 14 Days Following Receipt of Each Dose of DENGVAXIA or Placebo in Children and Adolescents 9 through 16 Years of Age in Study 1
 |  | Dose 1 |  | Dose 2 |  | Dose 3
 |  | DENGVAXIA % N = 1,264–1,326 | Placebo % N = 635–657 | DENGVAXIA % N = 1,228–1,298 | Placebo % N = 594–639 | DENGVAXIA % N = 1,215–1,279 | Placebo % N = 597–631
Injection Site Reactions
Pain [For subjects 9 through 11 years of age – Grade 3: Incapacitating, unable to perform usual activities. For subjects 12 through 16 years of age – Grade 3: Significant; prevents daily activity.] | Any Grade 3 | 32.4 0.8 | 26.3 0.9 | 25.6 0.5 | 16.4 0.0 | 22.5 0.9 | 16.5 0.3
Erythema [For subjects 9 through 11 years of age – Grade 3: ≥50 mm. For subjects 12 through 16 years of age – Grade 3: >100 mm.] | Any Grade 3 | 4.1 0.0 | 4.7 0.2 | 1.9 <0.1 | 1.7 0.0 | 1.5 0.0 | 1.6 0.0
Swelling | Any Grade 3 | 3.5 0.0 | 2.7 0.2 | 1.9 0.0 | 0.9 0.0 | 1.6 0.0 | 1.3 0.0
Systemic Adverse Reactions
Asthenia [For all subjects – Grade 3: Significant; prevents daily activity.] | Any Grade 3 | 24.6 2.7 | 22.5 2.6 | 17.8 1.8 | 16.4 1.1 | 16.3 1.3 | 17.4 1.3
Fever [For all subjects – Any Fever: ≥38.0°C. Grade 3: ≥39.0°C.] | Any Grade 3 | 6.8 1.7 | 6.6 1.1 | 5.9 0.8 | 7.1 1.2 | 7.3 1.1 | 8.7 0.8
Headache | Any Grade 3 | 39.9 5.1 | 41.6 4.1 | 29.8 2.1 | 28.5 2.3 | 29.6 2.6 | 25.0 1.9
Malaise | Any Grade 3 | 24.5 2.4 | 25.9 2.3 | 20.8 1.3 | 16.6 1.3 | 19.3 1.4 | 15.2 1.1
Myalgia | Any Grade 3 | 29.2 2.2 | 27.4 1.5 | 21.0 1.6 | 15.8 0.8 | 20.0 1.5 | 18.4 0.8
N: range number of subjects with available data for the specified endpoints
Study 1, NCT01374516
Placebo: 0.9% sodium chloride

Table 2: Percentages of Subjects with Solicited Injection Site Reactions within 7 Days and Systemic Adverse Reactions within 14 Days Following Receipt of Each Dose of DENGVAXIA or Placebo in Children and Adolescents 6 through 8 years and 9 through 14 Years of Age in Study 2
 |  | Dose 1 |  | Dose 2 |  | Dose 3
 |  | DENGVAXIA % | Placebo % | DENGVAXIA % | Placebo % | DENGVAXIA % | Placebo %
6–8 years
 |  | N = 254 | N = 127 | N = 253 | N = 126 | N = 251 | N = 125
Injection Site Reactions
Pain [For subjects 6 through 11 years of age – Grade 3: Incapacitating, unable to perform usual activities. For subjects 12 through 14 years of age – Grade 3: Significant; prevents daily activity.] | Any Grade 3 | 28.3 0.0 | 26.8 0.0 | 26.5 0.0 | 19.0 0.0 | 23.1 0.0 | 23.2 0.0
Erythema [For subjects 6 through 11 years of age – Grade 3: ≥50 mm. For subjects 12 through 14 years of age – Grade 3: >100 mm.] | Any Grade 3 | 7.9 0.0 | 7.9 0.0 | 4.7 0.0 | 5.6 0.0 | 5.6 0.0 | 3.2 0.0
Swelling | Any Grade 3 | 5.5 0.0 | 3.1 0.0 | 4.0 0.0 | 2.4 0.0 | 3.2 0.0 | 3.2 0.0
Systemic Adverse Reactions
Asthenia [For all subjects – Grade 3: Significant; prevents daily activity.] | Any Grade 3 | 12.6 0.8 | 9.4 2.4 | 9.5 0.4 | 9.5 1.6 | 6.8 0.0 | 12.8 0.0
Fever [For all subjects – Any Fever: ≥38.0°C. Grade 3: ≥39.0°C.] | Any Grade 3 | 8.3 1.2 | 7.1 1.6 | 9.1 1.2 | 4.8 1.6 | 5.2 0.8 | 4.8 0.0
Headache | Any Grade 3 | 27.2 0.4 | 21.3 1.6 | 19.4 2.4 | 15.1 1.6 | 17.9 0.4 | 20.0 0.0
Malaise | Any Grade 3 | 18.5 0.8 | 13.4 1.6 | 13.0 0.4 | 12.7 0.8 | 11.6 0.8 | 16.0 0.0
Myalgia | Any Grade 3 | 15.0 0.0 | 13.4 0.8 | 12.6 0.4 | 10.3 0.0 | 10.0 0.0 | 12.8 0.0
9–14 years
 |  | N = 617 | N = 311 | N = 614 | N = 309–310 | N = 607–611 | N = 309
Injection Site Reactions
Pain | Any Grade 3 | 30.5 0.0 | 27.0 0.0 | 19.4 0.0 | 17.4 0.0 | 20.3 0.0 | 15.2 0.0
Erythema | Any Grade 3 | 2.1 0.0 | 1.6 0.0 | 2.0 0.0 | 1.0 0.0 | 1.1 0.0 | 0.6 0.0
Swelling | Any Grade 3 | 1.5 0.0 | 1.9 0.0 | 1.0 0.0 | 0.6 0.0 | 0.3 0.0 | 0.3 0.0
Systemic Adverse Reactions
Asthenia | Any Grade 3 | 20.3 0.3 | 17.0 0.3 | 13.7 0.5 | 11.6 0.3 | 12.8 0.5 | 12.9 0.6
Fever | Any Grade 3 | 4.5 0.6 | 4.8 0.6 | 4.9 1.1 | 5.8 0.3 | 5.1 0.7 | 5.2 0.3
Headache | Any Grade 3 | 33.9 1.0 | 29.3 1.0 | 20.5 0.7 | 21.0 0.3 | 18.3 0.7 | 18.8 0.3
Malaise | Any Grade 3 | 24.8 0.6 | 25.4 0.3 | 15.0 0.7 | 16.1 0.3 | 15.1 0.7 | 17.8 0.3
Myalgia | Any Grade 3 | 21.4 0.2 | 22.2 0.0 | 13.8 0.2 | 15.2 0.0 | 13.6 0.5 | 12.3 0.0
N: range number of subjects with available data for the specified endpoints
Study 2, NCT01373281
Placebo: 0.9% sodium chloride

Unsolicited Non-serious Adverse Reactions

In Study 1, 1.2% of subjects in the DENGVAXIA group (16/1,333) and 0.8% of subjects in the placebo group (5/664) reported at least 1 unsolicited non-serious adverse reaction within 28 days following any dose.

In this study, 0.7% of the subjects in the DENGVAXIA group and 0.5% in the placebo group reported at least one unsolicited non-serious injection site adverse reaction. The unsolicited non-serious adverse reactions were injection site pain (after 7 days following any dose), hematoma, pruritus and anesthesia in the vaccine group and pain and induration in the placebo group.

In this study, 0.5% of the subjects in the DENGVAXIA group and 0.3% in the placebo group reported at least one unsolicited non-serious systemic adverse reaction. The unsolicited non-serious systemic adverse reactions were malaise, abdominal pain, vomiting, dyspnea, generalized erythema, vertigo, asthma crisis and urticaria in the vaccine group and pruritus and lymphadenitis in the placebo group.

Most unsolicited non-serious adverse reactions started within 3 days of any injection and resolved within 3 days or less.

A total of 2 subjects (one subject with asthma crisis and urticaria occurring the day of the first dose, and one subject with malaise occurring 20 days after the first dose) in the DENGVAXIA group (0.2%) and none in the placebo group reported unsolicited non-serious Grade 3 (significant; prevents daily activity) adverse reactions.

In Study 2, 0.8% of the subjects in the DENGVAXIA group and 0.2% in the placebo group reported at least one unsolicited non-serious injection site adverse reaction. The unsolicited non-serious adverse reactions following DENGVAXIA were injection site pain (after 7 days following any dose), discoloration, pruritus and hematoma.

In this study, 0.9% of the subjects in the DENGVAXIA group and 0.7% in the placebo group reported at least one unsolicited non-serious systemic adverse reaction. The unsolicited non-serious systemic adverse reactions following DENGVAXIA were malaise, urticaria, and dizziness.

Most unsolicited non-serious adverse reactions started within 3 days of any injection and resolved within 3 days or less.

No subjects in the DENGVAXIA group or in the placebo group reported unsolicited non-serious Grade 3 (significant; prevents daily activity) adverse reactions.

Severe Dengue Following Vaccination with DENGVAXIA and Subsequent Dengue Infection

Subjects were monitored for severe dengue from Day 0 (day of first study vaccination) to month 72 (after first study vaccination) in three multi-center, observer-blind, randomized (2:1), placebo-controlled trials conducted in Latin America and Puerto Rico (Study 1, NCT01374516) and the Asia-Pacific region (Study 2, NCT01373281; Study 3, NCT00842530). A subset of 3,203 subjects (80.1%) enrolled in Study 3 were re-consented to participate in an extension study to evaluate safety of DENGVAXIA for 72 months (Study 4, NCT01983553). A total of 21,295 children and adolescents 6 through 16 years of age enrolled in these trials received at least one dose of DENGVAXIA. Table 3 presents the incidences and hazard ratios of severe dengue from month 13 to month 72 post vaccination with DENGVAXIA or placebo in children and adolescents 6 through 16 years of age, by dengue baseline serostatus. An increased rate of severe dengue was observed following vaccination with DENGVAXIA and subsequent infection with any dengue virus serotype in persons not previously infected by dengue virus. [See Warnings and Precautions (5.1).]

Table 3: Number of Events and Incidence of Severe Dengue [Severe Dengue according to IDMC (Independent Data Monitoring Committee) definition: Proven dengue fever (2 days fever + virological confirmation) plus one of the following: (a) Platelet count ≤100,000/μL and bleeding plus plasma leakage (effusion on chest x-ray [CXR] or clinically apparent ascites including imaging procedures or hematocrit ≥20% above baseline recovery level or standard for age if only one reading); (b) shock; (c) bleeding (requiring blood transfusion); (d) encephalopathy; (e) liver impairment; (f) impaired kidney function; (g) myocarditis, pericarditis or clinical heart failure.] From Month 13 to Month -72 in Children 6 through 16 Years of Age, by Previous Dengue Infection Status, in Studies 1, 2, 3, and 4
Dengue Infection Status at Month 13 [Based on measured Dengue anti-NS1 IgG ELISA at month 13 from first vaccination (Dengue Seropositive= ≥9EU/mL).] | DENGVAXIA n (Incidence [Cumulative incidence over 5 years from 13 months after the first vaccination.] , %) | Placebo n (Incidence, %) | Hazard Ratio of Severe Dengue (95% CI)
Previous Dengue Infection (Dengue Seropositive at Month 13) | 19 (0.127) | 39 (0.531) | 0.23 (0.13; 0.40)
No Previous Dengue Infection (Dengue Seronegative at Month 13) | 22 (0. 586) | 3 (0.152) | 3.94 (1.17; 13.27)
n: number of subjects with severe dengue cases
CI: confidence interval
Study 1, NCT01374516; Study 2, NCT01373281; Study 3, NCT00842530; Study 4, NCT01983553

Non-fatal Serious Adverse Events

In 12 studies conducted among subjects 6 through 16 years of age (NCT 01374516, NCT01373281, NCT00842530, NCT00993447, NCT00875524, NCT00788151, NCT00880893, NCT01187433, NCT01254422, NCT02628444, NCT02993757, NCT02979535), subjects were monitored for serious adverse events (SAEs) for at least 6 months after the last dose of DENGVAXIA.

In these 12 studies, all of which monitored SAEs within 28 days, the proportions of subjects who reported at least 1 non-fatal SAE within 28 days following any dose were 0.7% (168/22,924) in the DENGVAXIA group and 0.9% (98/10,668) in the placebo group. The following events were considered related to DENGVAXIA: asthma attack (day of Dose 1), urticaria (day of Dose 2), convulsion (day of Dose 1) and acute disseminated encephalomyelitis (7 days post Dose 1).

In the 12 studies with subjects monitored for 6 months after the last dose, the proportions of subjects who reported at least 1 non-fatal SAE after 28 days and up to 6 months after any dose were similar in the 2 groups: 3.2% in the DENGVAXIA group (728/22,924) and 3.8% in the placebo group (404/10,668). None of these SAEs were considered related to the vaccination.

Deaths

From the first administered dose up to month 72, 53 deaths (0. 2%) for subjects who received DENGVAXIA and 34 deaths (0.3 %) for subjects who received placebo were reported in 9 of the 12 studies conducted among subjects 6 through 16 years of age with at least 6 months follow-up. None of the deaths were considered related to vaccination. Causes of death among subjects were consistent with those generally reported in children and adolescent populations.

6.2 Postmarketing Experience

In addition to events reported in clinical trials for DENGVAXIA, the following adverse events have been spontaneously reported during postapproval use. Because these events are reported voluntarily from a population of uncertain size, it is not always possible to reliably estimate their frequency or establish a causal relationship to the vaccine.

The following adverse events were included based on one or more of the following factors: severity, frequency of reporting, or strength of evidence for a causal relationship to DENGVAXIA.

Immune system disorders

Allergic including anaphylactic reactions.

Infections and infestations

Severe dengue infection, including hospitalization and death, in individuals for whom dengue infection status prior to vaccination was unknown and who were subsequently infected with dengue following vaccination.

7 DRUG INTERACTIONS

7.1 Immunosuppressive Treatments

Immunosuppressive therapies, including irradiation, antimetabolites, alkylating agents, cytotoxic drugs and corticosteroids (used in greater than physiologic doses), may reduce the immune response to DENGVAXIA.

7.2 Drug/Laboratory Test Interactions

DENGVAXIA may cause temporary depression of tuberculin purified protein derivative (PPD) test sensitivity, leading to false negative results. Tuberculin testing should be performed before DENGVAXIA is administered or at least 1 month following vaccination with DENGVAXIA.

8 USE IN SPECIFIC POPULATIONS

8.1 Pregnancy

Pregnancy Exposure Registry

There is a pregnancy exposure registry that monitors pregnancy outcomes in women exposed to DENGVAXIA during pregnancy. Women who receive DENGVAXIA during pregnancy are encouraged to contact directly, or have their healthcare professional contact, Sanofi Pasteur Inc. at 1-800-822-2463 (1-800-VACCINE) to enroll in or obtain information about the registry.

Risk Summary

All pregnancies have a risk of birth defect, loss, or other adverse outcomes. In the US general population, the estimated background risk of major birth defects and miscarriage in clinically recognized pregnancies is 2% to 4% and 15% to 20%, respectively.

No specific studies of DENGVAXIA have been performed among pregnant women. A limited number of cases of inadvertent exposure during pregnancy were reported during clinical studies. Isolated adverse pregnancy outcomes (e.g., stillbirth, intrauterine death, spontaneous abortion, blighted ovum) have been observed for these exposed pregnancies, with similar frequency and nature in the vaccinated individuals compared to the control group, and with risk factors identified for all cases. Available data in pregnant women are not sufficient to determine the effects of DENGVAXIA on pregnancy, embryo-fetal development, parturition and postnatal development.

In two developmental toxicity studies, the effect of DENGVAXIA on embryo-fetal and postnatal development was evaluated in pregnant rabbits and mice. A developmental toxicity study was performed in female rabbits given a 5 log10 50% cell culture infectious dose (CCID50) of DENGVAXIA (full human dose ranging from 4.5 log10 to 6.0 log10 CCID50) by intravenous injection prior to mating and during gestation. The study revealed no evidence of harm to the fetus due to DENGVAXIA. In another study, female mice were administered a single dose of 5 log10 CCID50, 6.5 log10 CCID50 (about 3 times the highest human dose) or 8 log10 CCID50 (about 100 times the highest human dose) of DENGVAXIA by intravenous injection during gestation. Fetal toxicities were observed at maternally toxic doses. [See Animal Data (8.1).]

Clinical Considerations

Disease-associated maternal and/or embryo/fetal risk

Pregnant women are at increased risk of complications associated with dengue infection compared to non-pregnant women. Pregnant women with dengue may be at increased risk for adverse pregnancy outcomes, including preterm labor and delivery. Vertical transmission of dengue virus from mothers with viremia at delivery to their infants has been reported.

Fetal/neonatal adverse reactions

Vaccine viremia can occur 7 to 14 days after vaccination with a duration of <7 days [See Pharmacokinetics (12.3).]. The potential for transmission of the vaccine virus from mother to infant is unknown.

Animal Data

In two developmental toxicity studies, the effect of DENGVAXIA on embryo-fetal and postnatal development was evaluated in pregnant rabbits and mice.

Rabbits were administered a full human dose [0.5 mL (5 log10 CCID50/animal/occasion)] of DENGVAXIA by intravenous injection 30 and 10 days before mating and on Days 6, 12 and 27 during gestation. No vaccine-related fetal malformation or variations and adverse effects on female fertility or preweaning development were reported in this study. Pregnant mice were administered a single dose of either 5 log10 CCID50 (full human dose ranging from 4.5 log10 to 6.0 log10 CCID50), 6.5 log10 CCID50 (about 3 times the highest human dose) or 8 log10 CCID50 (about 100 times the highest human dose) of DENGVAXIA by intravenous injection on Day 6, 9 or 12 of gestation. At doses of 6.5 log10 CCID50 or 8 log10 CCID50 of DENGVAXIA, maternal toxicity was observed which was associated with increased postimplantation loss and at doses of 8 log10 CCID50 with reduced fetal body weight. The significance of this observation for humans is unknown, especially considering the different route of administration (the human route of administration is subcutaneous) and dose levels which exceeded the intended human dose. There were no vaccine related fetal malformations or other evidence of teratogenesis noted in this study.

8.2 Lactation

Risk Summary

Human data are not available to assess the impact of DENGVAXIA on milk production, its presence in breast milk, or its effects on the breastfed child. The developmental and health benefits of breastfeeding should be considered along with the mother's clinical need for DENGVAXIA and any potential adverse effects on the breastfed child from DENGVAXIA or from the underlying maternal condition. For preventive vaccines, the underlying condition is susceptibility to disease prevented by the vaccine. A lactation study in which female mice were administered a single dose of DENGVAXIA on day 14 of lactation did not show the presence of DENGVAXIA in breast milk.

Clinical Considerations

Disease-associated maternal and/or embryo/fetal risk

Vertical transmission of dengue virus, including potentially through breastmilk, has been reported.

Fetal/neonatal adverse reactions

Vaccine viremia can occur 7 to 14 days after vaccination with a duration of <7 days. [See Pharmacokinetics (12.3).] The potential for transmission of the vaccine virus from mother to infant through breastmilk is unknown.

Animal Data

A developmental toxicity study in which female mice were administered a single injection of 5 log10 CCID50 (full human dose ranging from 4.5 log10 to 6.0 log10 CCID50), 6.5 log10 CCID50 or 8 log10 CCID50 of DENGVAXIA by intravenous injection on Day 14 of lactation did not show the presence of DENGVAXIA in breast milk in mice when measured 24 hours after vaccine administration.

8.4 Pediatric Use

DENGVAXIA is not approved for use in individuals younger than 6 years of age. Evidence from clinical studies strongly suggests that DENGVAXIA would be unsafe in individuals younger than 6 years of age because of an increased risk of severe and hospitalized dengue regardless of dengue serostatus. [See Warnings and Precautions (5.1)]

8.5 Geriatric Use

Safety and effectiveness of DENGVAXIA in adults 65 years of age and older have not been established.

11 DESCRIPTION

DENGVAXIA (Dengue Tetravalent Vaccine, Live) is a sterile suspension for subcutaneous injection. DENGVAXIA is supplied as a vial of lyophilized vaccine antigen, which must be reconstituted at the time of use with 0.6 mL from the accompanying vial of diluent (0.4% sodium chloride). After reconstitution, DENGVAXIA is a clear, colorless suspension (trace amounts of white to translucent proteinaceous particles may be present). [See Dosage and Administration (2.3).]

After reconstitution, each 0.5 mL dose of DENGVAXIA contains 4.5 – 6.0 log10 CCID50 of each of the chimeric yellow fever dengue (CYD) virus serotypes 1, 2, 3, and 4. Each 0.5 mL dose is formulated to contain 2 mg sodium chloride and the following ingredients as stabilizers: 0.56 mg essential amino acids (including L-phenylalanine), 0.2 mg non-essential amino acids, 2.5 mg L-arginine hydrochloride, 18.75 mg sucrose, 13.75 mg D-trehalose dihydrate, 9.38 mg D-sorbitol, 0.18 mg trometamol, and 0.63 mg urea.

Each of the four CYD viruses (CYD-1, CYD-2, CYD-3, and CYD-4) in DENGVAXIA was constructed using recombinant DNA technology by replacing the sequences encoding the pre-membrane (prM) and envelope (E) proteins in the yellow fever (YF) 17D204 vaccine virus genome with those encoding for the homologous sequences of dengue virus serotypes 1, 2, 3, and 4, respectively. Each CYD virus is cultured separately in Vero cells (African Green Monkey kidney) under serum-free conditions, harvested from the supernatant of the Vero cells and purified by membrane chromatography and ultrafiltration. The purified and concentrated harvest of each CYD virus is then diluted in a stabilizer solution to produce the four monovalent drug substances. The final bulk product is a mixture of the four monovalent drug substances diluted in the stabilizer solution. The final bulk product is sterilized by filtration at 0.22 µm, filled into vials and freeze-dried.

DENGVAXIA does not contain preservative.

The vial stoppers for the Lyophilized Vaccine Antigen and Diluent vials of DENGVAXIA are not made with natural rubber latex.

12 CLINICAL PHARMACOLOGY

12.1 Mechanism of Action

Following administration, DENGVAXIA elicits dengue-specific immune responses against the four dengue virus serotypes. The exact mechanism of protection has not been determined.

12.3 Pharmacokinetics

Viremia

In studies that evaluated the occurrence of vaccine viremia systematically at pre-specified timepoints, vaccine viremia (measured by genomic amplification methods) was observed following vaccination with DENGVAXIA in 5.6% of subjects, with 90% of these occurrences documented after the first injection. Vaccine viremia was observed 7 to 14 days after DENGVAXIA vaccination with a duration of <7 days.

13 NONCLINICAL TOXICOLOGY

13.1 Carcinogenesis, Mutagenesis, Impairment of Fertility

DENGVAXIA has not been evaluated for carcinogenic or mutagenic potential or impairment of male fertility. Exposure of female rabbits to DENGVAXIA prior to and during gestation did not impair fertility. [See Use in Specific Populations (8.1).]

14 CLINICAL STUDIES

14.1 Efficacy

The efficacy of DENGVAXIA was evaluated in two randomized, observer-blind, placebo-controlled, multi-center studies. Study 1 (N=20,869) was conducted in individuals 9 through 16 years of age in four Latin American countries and Puerto Rico; and Study 2 (N=10,275) was conducted in individuals 2 through 14 years of age in five Asia-Pacific countries. A subset of subjects in each study (10% in Study 1; 20% in Study 2) was evaluated for antibodies to dengue virus at the time of enrollment and at later time points. Both studies enrolled subjects irrespective of evidence of previous dengue infection. Subjects were randomized 2:1 to receive either DENGVAXIA or saline placebo and were monitored for symptomatic virologically confirmed dengue (VCD) starting at Day 0. Per protocol vaccine efficacy was assessed beginning 28 days after the third vaccination for 12 months. VCD was defined as an acute febrile illness (temperature ≥38°C on at least 2 consecutive days) virologically confirmed by dengue RT-PCR and/or dengue non-structural protein 1 (NS1) ELISA Antigen Test. For each study, in pre-specified vaccine efficacy analyses including the full age range of subjects enrolled, the pre-specified criterion for demonstrating efficacy of DENGVAXIA against VCD due to any dengue virus serotype and irrespective of previous dengue virus infection, was met (lower bound of 95% CI for vaccine efficacy >25%). These studies were not designed to demonstrate efficacy of DENGVAXIA against individual dengue serotypes.

Given the identification of the increased risk for severe dengue following vaccination with DENGVAXIA and subsequent infection with dengue virus in persons not previously infected with dengue virus [see Adverse Reactions (6.1)], Table 4 presents analyses of vaccine efficacy against VCD due to any dengue virus serotype, limited to subjects who had baseline sera evaluated and who were dengue seropositive at baseline. These analyses include subjects 9 through 16 years of age from Study 1 and subjects 6 through 14 years of age from Study 2.

Table 4: Efficacy of DENGVAXIA against Symptomatic VCD in Subjects Seropositive for Dengue at Baseline from 28 Days Post Dose 3 for a Period of 12 Months – Study 1 (Ages 9 through 16 Years) and Study 2 (Ages 6 through 14 Years) – mFASE [mFASE (Modified Full Analysis Set): Set of the subjects who received 3 injections as per randomization including those with protocol deviations.] – Subjects Included in the Immunogenicity Subset
 | DENGVAXIA group Cases (Subjects) | Placebo group Cases (Subjects) | VE % (95% CI) [VE is calculated as 1- ratio of density incidence of dengue between DENGVAXIA and Placebo groups.]
Study 1 (Subjects 9 through 16 years of age) | 7 (1034) | 17 (492) | 80.6 (50.7;93.2)
Study 2 (Subjects 6 through 14 years of age) | 6 (649) | 15 (337) | 79.5 (44.2;93.5)

14.2 Immunogenicity of Concomitantly Administered Vaccines

In a randomized, multicenter, open-label study (NCT02992418), 688 subjects aged from 9 through 60 years in the Philippines were randomized in a 1:1 ratio into two groups. In group 1, participants received Adacel concomitantly with the first dose of DENGVAXIA. In group 2, participants received Adacel followed by the first dose of DENGVAXIA one month later. A subgroup analysis was conducted including subjects 9 through 16 years of age who were dengue immune at baseline (Group 1 N=137, Group 2 N=133). There was no evidence of interference in the immune responses to Adacel when concomitantly administered with a first dose of DENGVAXIA as assessed by geometric mean concentrations of antibodies to the pertussis antigens contained in the vaccine and seroprotection rates for diphtheria and tetanus toxoids 28 days after vaccine administration. No information is available on the concomitant administration of Adacel and DENGVAXIA after the three-dose vaccination schedule.

Immune responses following the third dose of DENGVAXIA could not be assessed due to early termination of the study.

16 HOW SUPPLIED/STORAGE AND HANDLING

16.1 How Supplied

An outer package of 1 dose (NDC 49281-605-01) contains 1 single dose vial of Lyophilized Vaccine Antigen (NDC 49281-606-58) and 1 single dose vial of Saline Diluent (NDC 49281-549-58).

The vial stoppers for the Lyophilized Vaccine Antigen vials and the Saline Diluent vials of DENGVAXIA are not made with natural rubber latex.

16.2 Storage and Handling

Store Lyophilized Vaccine Antigen and Saline Diluent in a refrigerator at 2°C to 8°C (36°F to 46°F). Do not freeze. Protect from light.

Do not use after the expiration date shown on the vial labels of the Lyophilized Vaccine Antigen and Saline Diluent.

After reconstitution, administer DENGVAXIA immediately or store refrigerated at 2°C to 8°C (36°F to 46°F) and use within 30 minutes. Discard reconstituted vaccine if not used within 30 minutes.

17 PATIENT COUNSELING INFORMATION

Educate vaccine recipients regarding the most common adverse reactions that occur within 14 days following administration of DENGVAXIA (headache, injection site pain, malaise, asthenia, and myalgia).

Inform individuals to seek medical care if they develop signs and symptoms of dengue fever with particular attention to severe dengue warning signs (e.g., high fever, severe abdominal pain or tenderness, persistent vomiting, mucosal bleeding, somnolence and hyperactivity).

Register women who receive DENGVAXIA during pregnancy in the Pregnancy Registry by calling 1-800-822- 2463 (1-800-VACCINE). [See Pregnancy (8.1).]

Instruct vaccine recipients to report adverse reactions to their healthcare provider.

Manufactured and distributed by:
Sanofi Pasteur Inc.
Swiftwater PA 18370 USA

DENGVAXIA® is a registered trademark of Sanofi, its affiliates and/or its subsidiaries.

Adacel® is a registered trademark of Sanofi, its affiliates and/or its subsidiaries.©2023, Sanofi Pasteur Inc.- All rights reserved

PRINCIPAL DISPLAY PANEL - Kit Carton

NDC 49281-605-01

NOTICE: One vial of
Lyophilized Vaccine Antigen and
0.6 mL from the vial of Saline Diluent
MUST BE COMBINED BEFORE USE.

Dengue Tetravalent
Vaccine, Live
Dengvaxia®

Rx only

For 6 through 16 years of age

Contents (a single dose of Dengvaxia®):
1 vial containing Lyophilized Vaccine Antigen,
1 vial containing Saline Diluent (0.4% Sodium
Chloride). After reconstitution, a single dose of
Dengvaxia® is 0.5 mL.

SANOFI PASTEUR

PRINCIPAL DISPLAY PANEL - 0.5 mL Vial Label

Lyophilized Vaccine Antigen -
Reconstitute with Saline
Diluent (0.4% NaCl) to form
Dengvaxia®

0.5 mL Single Dose after Reconstitution
Subcutaneous use

Dengvaxia®
NDC 49281-606-58
Rx only

Mfd by: Sanofi Pasteur Inc.

L

7616

PRINCIPAL DISPLAY PANEL - 0.6 mL Vial Label

Saline Diluent
(0.4% Sodium Chloride)
NOT TO BE USED ALONE

Rx only

Add to 1 vial of
Lyophilized Vaccine
Antigen
to form Dengvaxia®